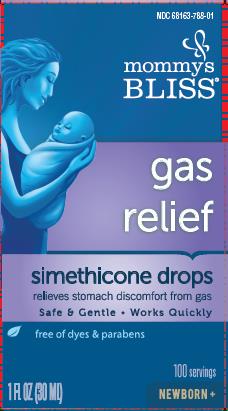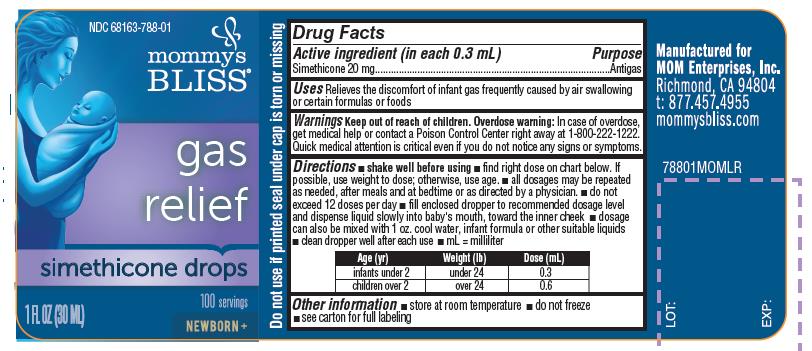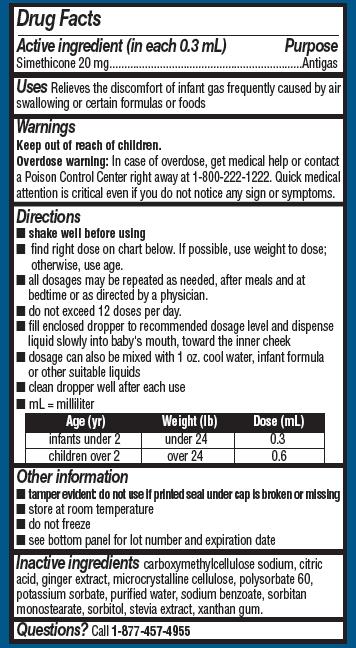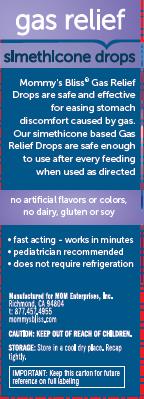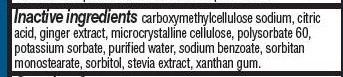 DRUG LABEL: simethicone gas relief
NDC: 71444-788 | Form: SUSPENSION/ DROPS
Manufacturer: MOM Enterprises, LCC
Category: otc | Type: HUMAN OTC DRUG LABEL
Date: 20240409

ACTIVE INGREDIENTS: DIMETHICONE 20 mg/0.3 mL
INACTIVE INGREDIENTS: GINGER; STEVIA LEAF; POTASSIUM SORBATE; CARBOXYMETHYLCELLULOSE SODIUM; ANHYDROUS CITRIC ACID; MICROCRYSTALLINE CELLULOSE; POLYSORBATE 60; SODIUM BENZOATE; SORBITOL; XANTHAN GUM; SORBITAN MONOSTEARATE; WATER

Mommy's Bliss Gas Relief Simethicone Drops